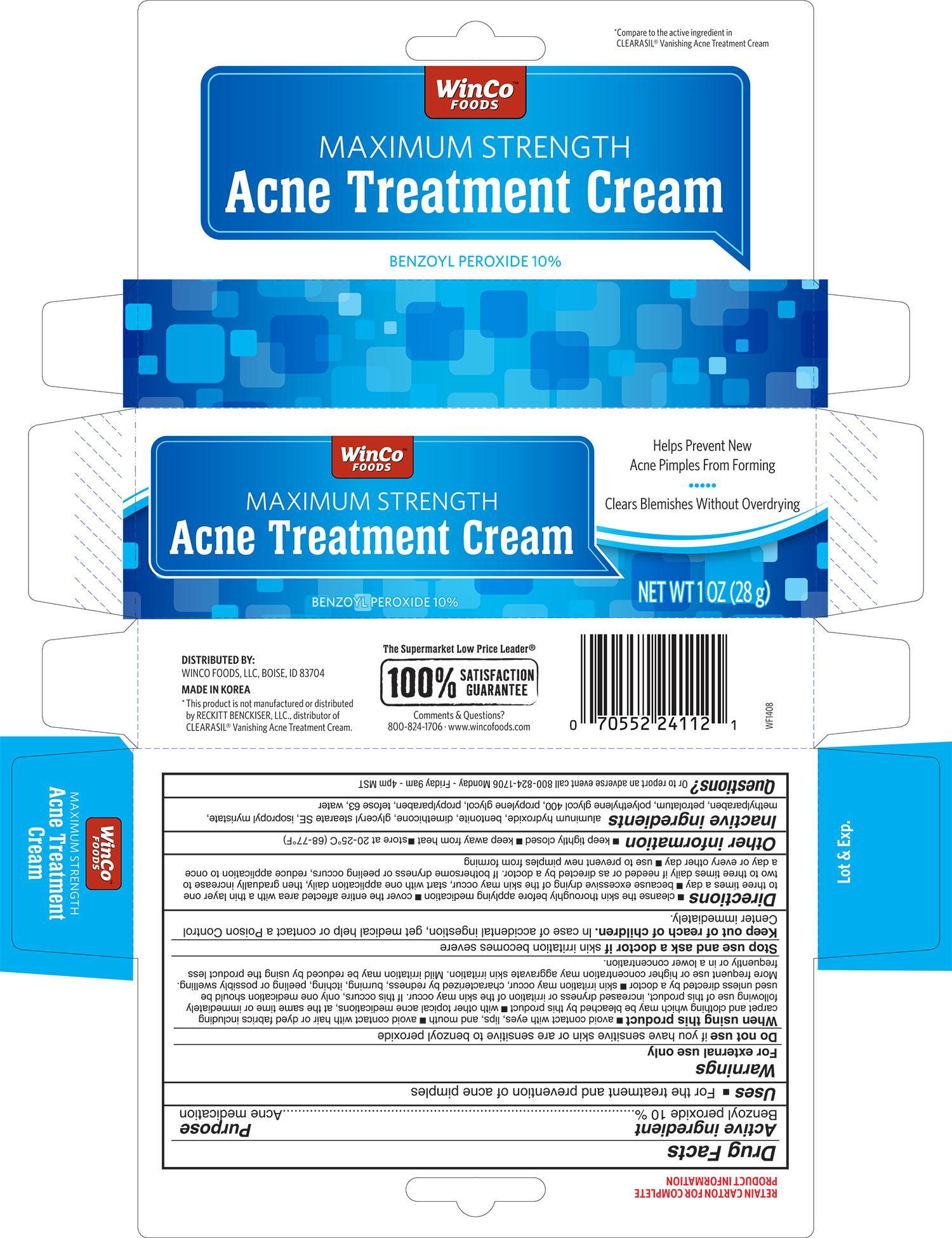 DRUG LABEL: WinCo Foods Maximum Strength Acne Treatment
NDC: 67091-195 | Form: CREAM
Manufacturer: WinCo Foods, LLC
Category: otc | Type: HUMAN OTC DRUG LABEL
Date: 20141201

ACTIVE INGREDIENTS: BENZOYL PEROXIDE 10 g/100 g
INACTIVE INGREDIENTS: ALUMINUM HYDROXIDE; BENTONITE; DIMETHICONE; GLYCERYL STEARATE SE; ISOPROPYL MYRISTATE; METHYLPARABEN; PETROLATUM; POLYETHYLENE GLYCOL 400; PROPYLPARABEN; WATER

Active ingredient Purpose

Benzoyl peroxide 10%..................................................... Acne medication

Uses

- For the treatmnet and prevention of acne pimples

Warnings

For external use only

Do not use if you have sensitive skin or are sensitive to benzoyl peroxide

When using this product

- avoid contact with eyes, lips, and mouth
- avoid contact with hair or dyed fabrics including carpet and clothing which may be bleached by this product
- with other topical acne medications, at the same time or immediately following use of this product, increased dryness or irritation of the skin may occur. If this occurs, only one medication should be used unless directed by a doctor
- skin irritation may occur, characterized by redness, burning, itching, peeling, or possibly swelling. More frequent use or higher concentration may aggravate skin irritation. Mild irritation may be reduced by using the product less frequently or in a lower concentration

Stop use and ask a doctor if skin irritation becomes severe

Keep out of reach of children. In case of accidental ingestion, get medical help or contact a Poison Control Center immediately

Directions

- cleanse the skin thoroughly before applying medication
- cover the entire affected area with a thin layer one to three times a day
- because excessive drying of the skin may occur, start with one application daily, then gradually increase to two to three times daily if needed or as directed by a doctor. If bothersome dryness or peeling occurs, reduce application to once a day or every other day
- use to prevent new pimples from forming

Other information

- keep tightly closed
- keep away from heat
- store at 20-25°C (68-77°F)

Inactive ingredients

aluminum hydroxide, bentonite, dimethicone, glyceryl stearate SE, isopropyl myristate, methylparaben, petrolatum, polyethylene glycol 400, propylene glycol, propylparaben, tefose 63, water

DOSAGE AND ADMINISTRATION

DISTRIBUTED BY:

WINCO FOODS, LLC

BOISE, ID 83704

MADE IN KOREA